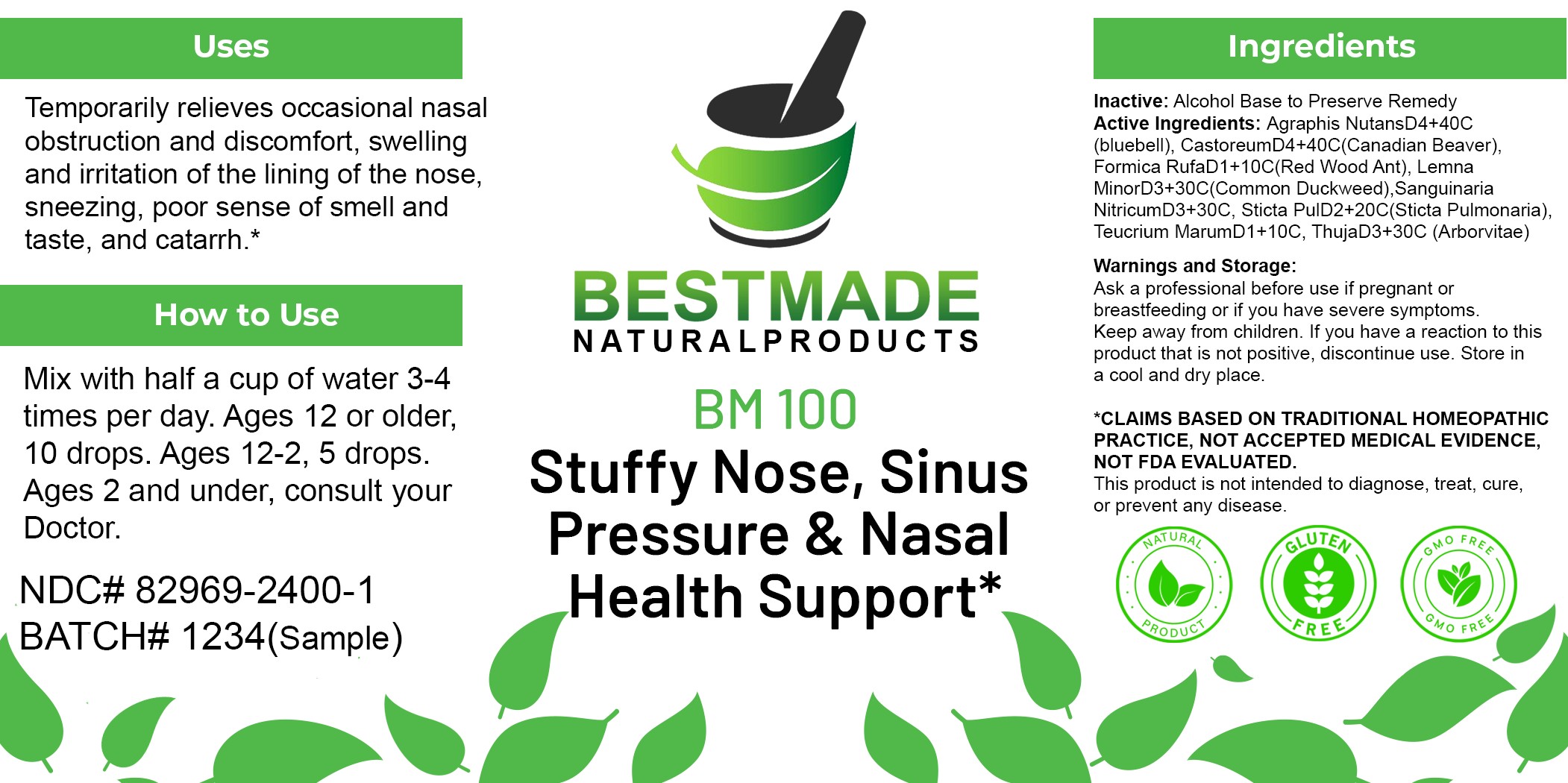 DRUG LABEL: BM100
NDC: 82969-2400 | Form: LIQUID
Manufacturer: Total Operations Management LLC DBA:Bestmade Natural Products Micro
Category: homeopathic | Type: HUMAN OTC DRUG LABEL
Date: 20250829

ACTIVE INGREDIENTS: FORMICA RUFA 10 [hp_C]/1 mL; THUJA OCCIDENTALIS LEAFY TWIG 30 [hp_C]/1 mL; CASTOR CANADENSIS SCENT GLAND SECRETION 40 [hp_C]/1 mL; LEMNA MINOR WHOLE 30 [hp_C]/1 mL; LOBARIA PULMONARIA 20 [hp_C]/1 mL; HYACINTHOIDES NON-SCRIPTA WHOLE 40 [hp_C]/1 mL; TEUCRIUM MARUM WHOLE 100 [hp_C]/1 mL
INACTIVE INGREDIENTS: ALCOHOL 0.96 mL/1 mL

BNP BM100

Uses
Temporarily relieves occasional nasal obstruction and discomfort, swelling and irritation of the lining of the nose, sneezing, poor sense of smell and taste, and catarrh.*

Uses
Temporarily relieves occasional nasal obstruction and discomfort, swelling and irritation of the lining of the nose, sneezing, poor sense of smell and taste, and catarrh.*

DOSAGE AND ADMINISTRATION

How to Use
Mix with half a cup of water 3-4 times per day. Ages 12 or older, 10 drops. Ages 12-2, 5 drops.
Ages 2 and under, consult your Doctor.

INACTIVE INGREDIENT

Ingredients

Inactive: Alcohol Base to Preserve Remedy

Active Ingredients:

Agraphis Nutans D4+40C (bluebell)

Castoreum D4+40C (Canadian Beaver)

Formica Rufa D1+10C (Red Wood Ant)

Lemna Minor D3+30C (Common Duckweed)

Sanguinaria Nitricum D3+30C

Sticta Pul D2+20C (Sticta Pulmonaria)

Teucrium Marum D1+10C

Thuja D3+30C (Arborvitae)

Warnings and Storage:
Ask a professional before use if pregnant or breastfeeding or if you have severe symptoms.
Keep away from children. If you have a reaction to this product that is not positive, discontinue use.
Store in a cool and dry place.

CLAIMS BASED ON TRADITIONAL HOMEOPATHIC PRACTICE, NOT ACCEPTED MEDICAL EVIDENCE, NOT FDA EVALUATED.
This product is not intended to diagnose, treat, cure, or prevent any disease.

KEEP OUT OF REACH OF CHILDREN

Warnings and Storage:
Ask a professional before use if pregnant or breastfeeding or if you have severe symptoms.
Keep away from children. If you have a reaction to this product that is not positive, discontinue use.
Store in a cool and dry place.

entire package label